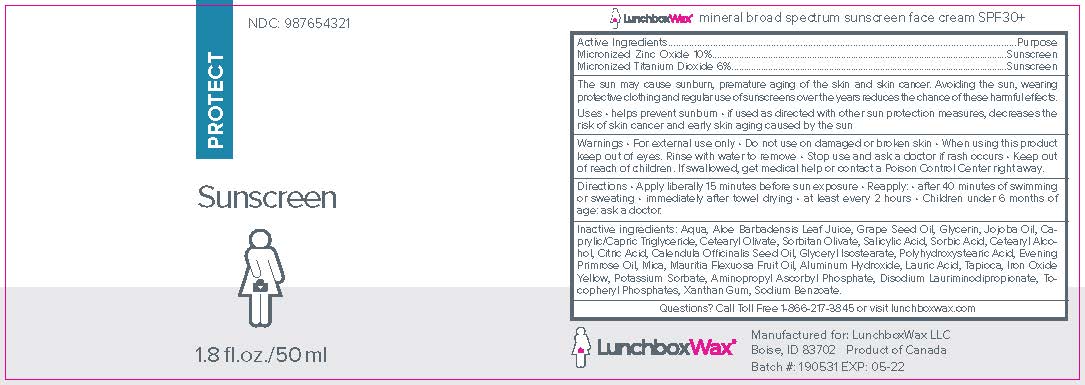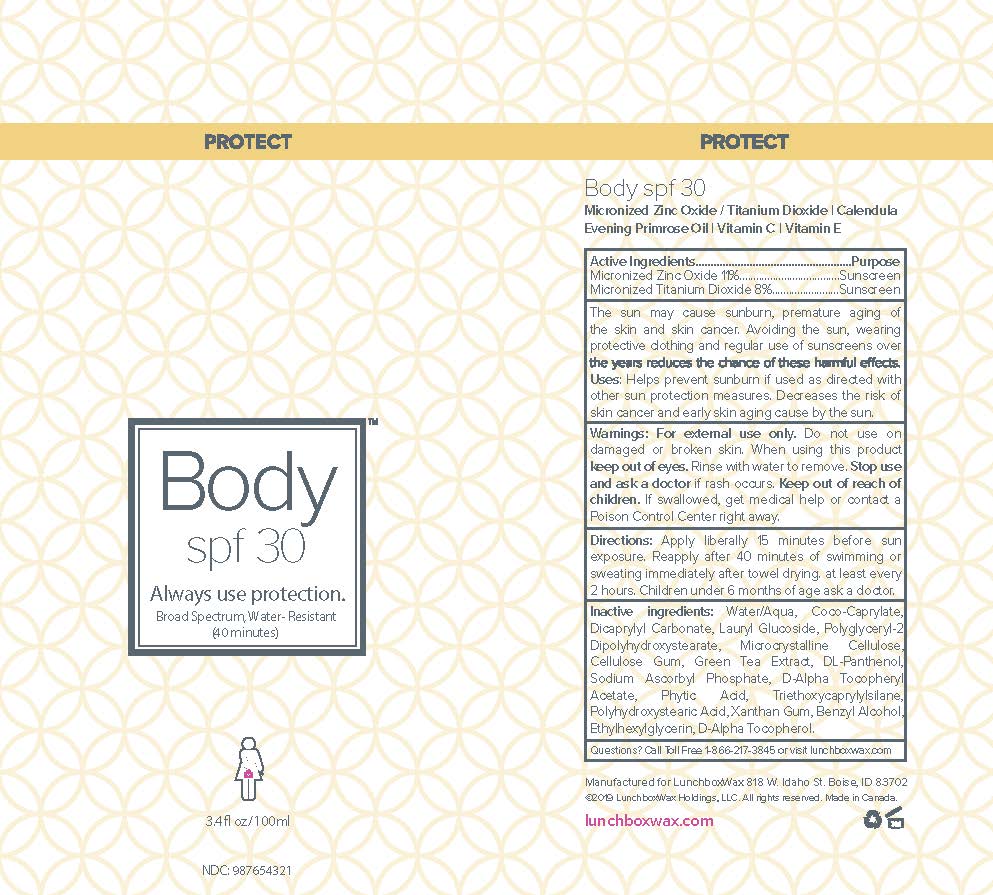 DRUG LABEL: Lunchboxwax mineral broad spectrum sunscreen face cream SPF30
NDC: 69711-371 | Form: CREAM
Manufacturer: Derma Soleil
Category: otc | Type: HUMAN OTC DRUG LABEL
Date: 20190909

ACTIVE INGREDIENTS: ZINC OXIDE 10 g/100 mL; TITANIUM DIOXIDE 6 g/100 mL
INACTIVE INGREDIENTS: MAURITIA FLEXUOSA FRUIT OIL; DISODIUM LAURIMINODIPROPIONATE TOCOPHERYL PHOSPHATES; SODIUM BENZOATE; CALENDULA OFFICINALIS SEED OIL; POLYHYDROXYSTEARIC ACID (2300 MW); LAURIC ACID; AMYLOSE, TAPIOCA; BROWN IRON OXIDE; POTASSIUM SORBATE; AMINOPROPYL ASCORBYL PHOSPHATE; GLYCERIN; WATER; XANTHAN GUM; EVENING PRIMROSE OIL; ALUMINUM HYDROXIDE; ANHYDROUS CITRIC ACID; GLYCERYL ISOSTEARATE; MICA; SORBITAN OLIVATE; ALOE VERA LEAF; SODIUM SALICYLATE; SORBIC ACID; GRAPE SEED OIL; JOJOBA OIL; CAPRYLIC/CAPRIC/LAURIC TRIGLYCERIDE; CETEARYL OLIVATE; CETOSTEARYL ALCOHOL

Lunchboxwax

LunchboxWax mineral broad spectrum sunscreen face cream SPF30+

PURPOSE

Micronized Zinc Oxide 10%..............Sunscreen

Micronized Titanium Dioxide 6%..............Sunscreen

ACTIVE INGREDIENT

Micronized Zinc 10%

Micronized Titanium Dioxide 6%

INDICATIONS AND USAGE

The sun may cause sunburn, premature aging of the skin and skin cancer. Avoiding the sun, wearing protective clothing and regular use of sunscreens over the years reduces the chance of these harmful effects.

Helps prevent sunburn

If used as directed with other sun protection measures, decreases the risk of skin cancer and early skin aging caused by sun

WARNINGS

For external use only.

Do not use on damaged or broken skin.

When using this product keep out of eyes. Rinse with water to remove.

Stop use and consult a doctor if rash occurs.

Keep out of reach of children.

If swallowed, get medical help or contact a Poison Control Center right away.

DOSAGE AND ADMINISTRATION

Apply liberally 15 minutes before sun exposure

Reapply

After 40 minutes of swimming or sweating

immediately after towel drying

at least every 2 hours

Children under 6 months of age: ask a doctor

INACTIVE INGREDIENT

Aqua, Aloe barbadensis Leaf Juice, Grape Seed Oil, Glycerine, Jojoba Oil,

Caprylic/Capric Triglyceride, Cetearyl Olivate, Sorbitan Olivate, Salicylic Acid, Sorbic Acid,

Cetearyl Alcohol, Citric Acid, Calendula officinalis Seed Oil, Glyceryl Isostearate,

Polyhydroxystearic Acid, Evening Primrose Oil, Mica, Mauritia flexuosa Fruit Oil, Aluminum Hydroxide,

Lauric Acid, Tapioca, Iron Oxide Yellow, Potassium Sorbate, Aminoprypyl Ascorbyl Phosphate,

Disodium Lauriminodipropionate Tocopheryl Phosphates, Xanthan Gum, Sodium Benzoate

Lunchboxwax Body SPF 30

PURPOSE

The sun may cause sunburn, premature aging of the skin and skin cancer. Avoiding the sun, wearing protective clothing and regular use of sunscreens over the years reduces the chance of these harmful effects. Users: Helps pprevent sunburn if used as directed with other sun protection measures. Decreases the risk of skin cancer and early skin aging cause by the sun.

ACTIVE INGREDIENT

Active Ingredients..........................................................Purpose

Micronized Zinc Oxide 11%..............................................Sunscreen

Micronized Titanium Dioxide 8%.......................................Sunscreen

INDICATIONS AND USAGE

The sun may cause sunburn, premature aging of the skin and skin cancer. Avoiding the sun, wearing protective clothing and regular use of sunscreens over the years reduces the chance of these harmful effects. Users: Helps pprevent sunburn if used as directed with other sun protection measures. Decreases the risk of skin cancer and early skin aging cause by the sun.

KEEP OUT OF REACH OF CHILDREN

Warnings: For external use only. Do not use on damaged or broken skin. When using this product

keep out of eyes. Rinse with water to remove. Stop use and ask a doctor if rash occurs. Keep out of reach of children. If swallowed, get medical help or contact a Poison Control Center right away.

WARNINGS

Warnings: For external use only. Do not use on damaged or broken skin. When using this product

keep out of eyes. Rinse with water to remove. Stop use and ask a doctor if rash occurs. Keep out of reach of children. If swallowed, get medical help or contact a Poison Control Center right away.

DOSAGE AND ADMINISTRATION

Direction: apply liberally 15 minutes before sun exposure. reapply after 40 minutes of swimming or sweating immediately after towel drying. at least every 2 hours. Children under 6 months of age ask a doctor

Inactive ingredients: Water/Aqua, Coco-Caprylate,
Dicaprylyl Carbonate, Lauryl Glucoside, Polyglyceryl-2
Dipolyhydroxystearate, Microcrystalline Cellulose,
Cellulose Gum, Green Tea Extract, DL-Panthenol,
Sodium Ascorbyl Phosphate, D-Alpha Tocopheryl
Acetate, Phytic Acid, Triethoxycaprylylsilane,
Polyhydroxystearic Acid, Xanthan Gum, Benzyl Alcohol,
Ethylhexylglycerin, D-Alpha Tocopherol.